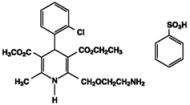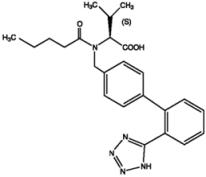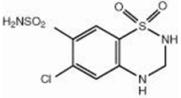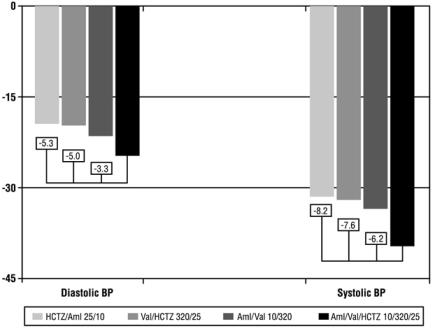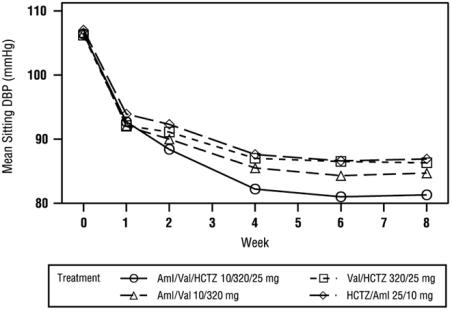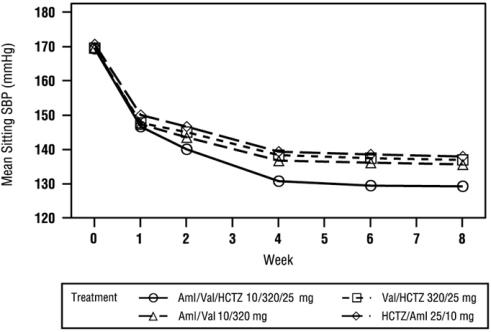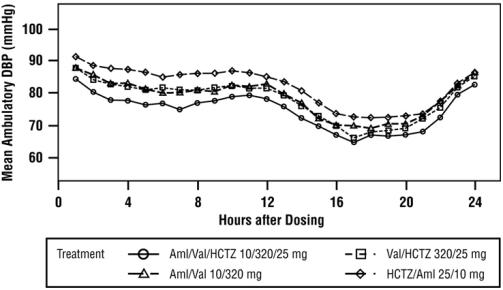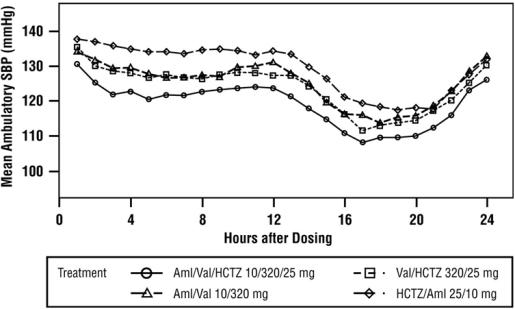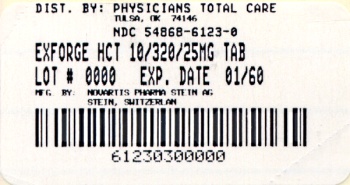 DRUG LABEL: Exforge HCT
NDC: 54868-6123 | Form: TABLET, FILM COATED
Manufacturer: Physicians Total Care, Inc.
Category: prescription | Type: HUMAN PRESCRIPTION DRUG LABEL
Date: 20111219

ACTIVE INGREDIENTS: AMLODIPINE BESYLATE 10 mg/1 1; VALSARTAN 320 mg/1 1; HYDROCHLOROTHIAZIDE 25 mg/1 1
INACTIVE INGREDIENTS: SILICON DIOXIDE; CROSPOVIDONE; HYPROMELLOSES; FERRIC OXIDE YELLOW; MAGNESIUM STEARATE; CELLULOSE, MICROCRYSTALLINE; TALC

HIGHLIGHTS OF PRESCRIBING INFORMATION

These highlights do not include all the information needed to use Exforge HCT safely and effectively. See full prescribing information for Exforge HCT.
Exforge HCT (amlodipine, valsartan, hydrochlorothiazide) Tablets
Initial U.S. Approval: 2009

RECENT MAJOR CHANGES

Warnings and Precautions: Acute Angle-Closure Glaucoma (5.11) 2/2011

WARNING: AVOID USE IN PREGNANCY

When pregnancy is detected, discontinue Exforge HCT as soon as possible. Drugs that act directly on the renin-angiotensin system can cause injury or death to the developing fetus. (5.1)

1 INDICATIONS AND USAGE

- Exforge HCT is for the treatment of hypertension (1)
- Not indicated for initial therapy

2 DOSAGE AND ADMINISTRATION

- Dose once-daily
- Exforge HCT may be used as add-on/switch therapy for patients not adequately controlled on any two of the following antihypertensive classes: calcium channel blockers, angiotensin receptor blockers, and diuretics.
- Exforge HCT may be substituted for its individually titrated components for patients on amlodipine, valsartan and hydrochlorothiazide (2).
- The full blood pressure lowering effect was achieved 2 weeks after being on the maximal dose of Exforge HCT (2).

3 DOSAGE FORMS AND STRENGTHS

Tablets: (amlodipine/valsartan/hydrochlorothiazide mg)

5/160/12.5

10/160/12.5

5/160/25

10/160/25

10/320/25 (3)

4 CONTRAINDICATIONS

- Anuria; Hypersensitivity to sulfonamide-derived drugs (4)

5 WARNINGS AND PRECAUTIONS

- Avoid fetal or neonatal exposure (5.1)
- Symptomatic hypotension with volume- or salt-depletion. Correct volume-depletion prior to administration (5.2)
- Increased angina and/or myocardial infarction (5.3)
- Avoid in patients with severely impaired hepatic (2.1, 5.4) or renal function (creatinine clearance ≤30 mL/min) (2.1, 5.5)
- Observe for signs of fluid or electrolyte imbalance (5.10)
- Thiazide diuretics may cause an exacerbation or activation of systemic lupus erythematosus (5.8)
- Hydrochlorothiazide has been associated with acute angle-closure glaucoma (5.11)

6 ADVERSE REACTIONS

Most common adverse events (≥2% incidence) are dizziness, peripheral edema, headache, dyspepsia, fatigue, muscle spasms, back pain, nausea and nasopharyngitis.

To report SUSPECTED ADVERSE REACTIONS, contact Novartis Pharmaceuticals Corporation at 1-888-669-6682 or FDA at 1-800-FDA-1088 or www.fda.gov/medwatch.

7 DRUG INTERACTIONS

Amlodipine:

- If simvastatin is co-administered with amlodipine, do not exceed doses greater than 20 mg daily of simvastatin (7)

Hydrochlorothiazide (7):

- Alcohol, barbiturates, narcotics: Potentiation of orthostatic hypotension
- Antidiabetic drugs: Dosage adjustment of antidiabetic may be required
- Cholestyramine and colestipol: Reduced absorption of thiazides
- Corticosteroids, ACTH: Hypokalemia, electrolyte depletion
- Lithium: Reduced renal clearance and high risk of lithium toxicity when used with diuretics. Should not be given with diuretics.
- NSAIDs: Can reduce diuretic, natriuretic and antihypertensive effects of diuretics.

8 USE IN SPECIFIC POPULATIONS

Pregnancy: Avoid use in pregnancy (5.1)

Nursing Mothers: Avoid use while nursing – discontinue either nursing or drug (8.3)

Geriatric Patients: No overall differences in the efficacy or safety of Exforge HCT was observed in this patient population, but greater sensitivity of some older individuals cannot be ruled out. (8.5)

FULL PRESCRIBING INFORMATION

WARNING: AVOID USE IN PREGNANCY

When pregnancy is detected, discontinue Exforge HCT as soon as possible. Drugs that act directly on the renin-angiotensin system can cause injury or death to the developing fetus [see Warnings and Precautions (5.1)].

1 INDICATIONS AND USAGE

Exforge HCT (amlodipine, valsartan, hydrochlorothiazide) is indicated for the treatment of hypertension.

This fixed combination drug is not indicated for the initial therapy of hypertension [see Dosage and Administration (2)].

2 DOSAGE AND ADMINISTRATION

2.1 General Considerations

Dose once-daily. The dosage may be increased after two weeks of therapy. The full blood pressure lowering effect was achieved 2 weeks after being on the maximal dose of Exforge HCT. The maximum recommended dose of Exforge HCT is 10/320/25 mg.

Exforge HCT may be administered with or without food.

No initial dosage adjustment is required for elderly patients.

Renal impairment: The usual regimens of therapy with Exforge HCT may be followed if the patient’s creatinine clearance is >30 mL/min. In patients with more severe renal impairment, loop diuretics are preferred to thiazides, so avoid use of Exforge HCT [see Impaired Renal Function (5.5)].

Hepatic impairment: Avoid Exforge HCT in patients with severe hepatic impairment. In patients with lesser degrees of hepatic impairment, monitor for worsening of hepatic or renal function and adverse reactions [see Impaired Hepatic Function (5.4)].

2.2 Add-on / Switch Therapy

Exforge HCT may be used for patients not adequately controlled on any two of the following antihypertensive classes: calcium channel blockers, angiotensin receptor blockers, and diuretics.

A patient who experiences dose-limiting adverse reactions to an individual component while on any dual combination of the components of Exforge HCT may be switched to Exforge HCT containing a lower dose of that component to achieve similar blood pressure reductions.

2.3 Replacement Therapy

Exforge HCT may be substituted for the individually titrated components.

3 DOSAGE FORMS AND STRENGTHS

- 5 mg amlodipine /160 mg valsartan /12.5 mg hydrochlorothiazide Tablets – White, non-scored, film-coated tablet, ovaloid, biconvex with beveled edge with debossing “NVR” on one side and “VCL” on the other side.
- 10 mg amlodipine /160 mg valsartan /12.5 mg hydrochlorothiazide Tablets – Pale yellow, non-scored, film-coated tablet, ovaloid, biconvex with beveled edge with debossing “NVR” on one side and “VDL” on the other side.
- 5 mg amlodipine /160 mg valsartan /25 mg hydrochlorothiazide Tablets – Yellow, non-scored, film-coated tablet, ovaloid, biconvex with beveled edge with debossing “NVR” on one side and “VEL” on the other side.
- 10 mg amlodipine /160 mg valsartan /25 mg hydrochlorothiazide Tablets – Brown-yellow, non-scored, film-coated tablet, ovaloid, biconvex with beveled edge with debossing “NVR” on one side and “VHL” on the other side.
- 10 mg amlodipine /320 mg valsartan /25 mg hydrochlorothiazide Tablets – Brown-yellow, non-scored, film-coated tablet, ovaloid, biconvex with beveled edge with debossing “NVR” on one side and “VFL” on the other side.

4 CONTRAINDICATIONS

Because of the hydrochlorothiazide component, Exforge HCT is contraindicated in patients with anuria or hypersensitivity to other sulfonamide-derived drugs.

5 WARNINGS AND PRECAUTIONS

5.1 Fetal/Neonatal Morbidity and Mortality

Exforge HCT can cause harm to the fetus when administered to a pregnant woman. If this drug is used during pregnancy, or if the patient becomes pregnant while taking this drug, the patient should be apprised of the potential hazard to the fetus.

Drugs that act on the renin angiotensin system can cause fetal and neonatal morbidity and mortality when used in pregnancy. In several dozen published cases, ACE inhibitor use during the second and third trimesters of pregnancy was associated with fetal and neonatal injury, including hypotension, neonatal skull hypoplasia, anuria, reversible or irreversible renal failure, and death [see Use in Specific Populations (8.1)].

5.2 Hypotension in Volume- or Salt-Depleted Patients

Excessive hypotension, including orthostatic hypotension, was seen in 1.7% of patients treated with the maximum dose of Exforge HCT (10/320/25 mg) compared to 1.8% of valsartan/HCTZ (320/25 mg) patients, 0.4% of amlodipine/valsartan (10/320 mg) patients, and 0.2% of HCTZ/amlodipine (25/10 mg) patients in a controlled trial in patients with moderate to severe uncomplicated hypertension. In patients with an activated renin-angiotensin system, such as volume- or salt-depleted patients receiving high doses of diuretics, symptomatic hypotension may occur in patients receiving angiotensin receptor blockers. Correct this condition prior to administration of Exforge HCT.

Exforge HCT has not been studied in patients with heart failure, recent myocardial infarction, or in patients undergoing surgery or dialysis. Patients with heart failure or post-myocardial infarction patients given valsartan commonly have some reduction in blood pressure, but discontinuation of therapy because of continuing symptomatic hypotension usually is not necessary when dosing instructions are followed. In controlled trials in heart failure patients, the incidence of hypotension in valsartan-treated patients was 5.5% compared to 1.8% in placebo-treated patients. In the Valsartan in Acute Myocardial Infarction Trial (VALIANT), hypotension in post-myocardial infarction patients led to permanent discontinuation of therapy in 1.4% of valsartan-treated patients and 0.8% of captopril-treated patients.

Since the vasodilation induced by amlodipine is gradual in onset, acute hypotension has rarely been reported after oral administration. Do not initiate treatment with Exforge HCT in patients with aortic or mitral stenosis or obstructive hypertrophic cardiomyopathy.

If excessive hypotension occurs with Exforge HCT, the patient should be placed in a supine position and, if necessary, given an intravenous infusion of normal saline. A transient hypotensive response is not a contraindication to further treatment, which usually can be continued without difficulty once the blood pressure has stabilized.

5.3 Increased Angina and/or Myocardial Infarction

Rarely, patients, particularly those with severe obstructive coronary artery disease, have developed documented increased frequency, duration or severity of angina or acute myocardial infarction upon starting calcium channel blocker therapy or at the time of dosage increase. The mechanism of this effect has not been elucidated.

5.4 Impaired Hepatic Function

Amlodipine is extensively metabolized by the liver and the plasma elimination half-life (t½) is 56 hours in patients with impaired hepatic function.

As the majority of valsartan is eliminated in the bile, patients with mild-to-moderate hepatic impairment, including patients with biliary obstructive disorders, showed lower valsartan clearance (higher AUCs).

In patients with impaired hepatic function or progressive liver disease, minor alterations of fluid and electrolyte balance, such as those resulting from diuretic use, may precipitate hepatic coma.

Therefore, avoid the use of Exforge HCT in patients with severe hepatic impairment. When administering Exforge HCT to patients with mild-to-moderate hepatic impairment, including patients with biliary obstructive disorders, monitor for worsening of hepatic or renal function, including fluid status and electrolytes, and adverse reactions.

5.5 Impaired Renal Function

As a consequence of inhibiting the renin-angiotensin-aldosterone system, changes in renal function may be anticipated in susceptible individuals. In patients with severe heart failure whose renal function may depend on the activity of the renin-angiotensin-aldosterone system, treatment with angiotensin-converting enzyme inhibitors and angiotensin receptor antagonists has been associated with oliguria and/or progressive azotemia and (rarely) with acute renal failure and/or death. Similar outcomes have been reported with valsartan.

In studies of ACE inhibitors in hypertensive patients with unilateral or bilateral renal artery stenosis, increases in serum creatinine or blood urea nitrogen have been reported. In a 4-day trial of valsartan in 12 hypertensive patients with unilateral renal artery stenosis, no significant increases in serum creatinine or blood urea nitrogen were observed. There has been no long-term use of valsartan in patients with unilateral or bilateral renal artery stenosis, but an effect similar to that seen with ACE inhibitors should be anticipated.

In patients with renal disease, thiazides may precipitate azotemia. Cumulative effects of the drug may develop in patients with impaired renal function.

Avoid use of Exforge HCT in severe renal disease (creatinine clearance ≤30 mL/min). The usual regimens of therapy with Exforge HCT may be followed if the patient’s creatinine clearance is >30 mL/min.

There is no experience in the use of Exforge HCT in patients with a recent kidney transplant.

5.6 Heart Failure

Exforge HCT has not been studied in patients with heart failure.

Studies with amlodipine: In general, calcium channel blockers should be used with close monitoring, including close follow-up of fluid status, electrolytes, renal function, and blood pressure in patients with heart failure. Amlodipine (5-10 mg per day) has been studied in a placebo-controlled trial of 1,153 patients with NYHA Class III or IV heart failure on stable doses of ACE inhibitor, digoxin, and diuretics. Follow-up was at least 6 months, with a mean of about 14 months. There was no overall adverse effect on survival or cardiac morbidity (as defined by life-threatening arrhythmia, acute myocardial infarction, or hospitalization for worsened heart failure). Amlodipine has been compared to placebo in four 8-12 week studies of patients with NYHA class II/III heart failure, involving a total of 697 patients. In these studies, there was no evidence of worsened heart failure based on measures of exercise tolerance, NYHA classification, symptoms, or LVEF.

Studies with valsartan: Some patients with heart failure have developed increases in blood urea nitrogen, serum creatinine, and potassium on valsartan. These effects are usually minor and transient, and they are more likely to occur in patients with pre-existing renal impairment. Dosage reduction and/or discontinuation of the diuretic and/or valsartan may be required. In the Valsartan Heart Failure Trial, in which 93% of patients were on concomitant ACE inhibitors, treatment was discontinued for elevations in creatinine or potassium (total of 1.0% on valsartan vs. 0.2% on placebo). In the Valsartan in Acute Myocardial Infarction Trial (VALIANT), discontinuation due to various types of renal dysfunction occurred in 1.1% of valsartan-treated patients and 0.8% of captopril-treated patients. Evaluation of patients with heart failure or post-myocardial infarction should always include assessment of renal function.

5.7 Hypersensitivity Reaction

Hypersensitivity reactions to hydrochlorothiazide may occur in patients with or without a history of allergy or bronchial asthma, but are more likely in patients with such a history.

5.8 Systemic Lupus Erythematosus

Thiazide diuretics have been reported to cause exacerbation or activation of systemic lupus erythematosus.

5.9 Lithium Interaction

Lithium generally should not be given with thiazides [see Drug Interactions, Hydrochlorothiazide, Lithium (7)].

5.10 Electrolytes and Metabolic Imbalances

Amlodipine -Valsartan - Hydrochlorothiazide

In the controlled trial of Exforge HCT in moderate to severe hypertensive patients, the incidence of hypokalemia (serum potassium <3.5 mEq/L) at any time post-baseline with the maximum dose of Exforge HCT (10/320/25 mg) was 10% compared to 25% with HCTZ/amlodipine (25/10 mg), 7% with valsartan/HCTZ (320/25 mg), and 3% with amlodipine/valsartan (10/320 mg). One patient (0.2%) discontinued therapy due to an adverse event of hypokalemia in each of the Exforge HCT and HCTZ/amlodipine groups. The incidence of hyperkalemia (serum potassium >5.7 mEq/L) was 0.4% with Exforge HCT compared to 0.2-0.7% with the dual therapies. Monitor serum electrolytes periodically based on Exforge HCT use and other factors such as renal function, other medications, or history of prior electrolyte imbalances.

Hydrochlorothiazide

All patients receiving thiazide therapy should be observed for clinical signs of fluid or electrolyte imbalance: hyponatremia, hypochloremic alkalosis, and hypokalemia. Serum and urine electrolyte determinations are particularly important when the patient is vomiting excessively or receiving parenteral fluids. Warning signs or symptoms of fluid and electrolyte imbalance, irrespective of cause, include dryness of mouth, thirst, weakness, lethargy, drowsiness, restlessness, confusion, seizures, muscle pains or cramps, muscular fatigue, hypotension, oliguria, tachycardia, and gastrointestinal disturbances such as nausea and vomiting.

Hypokalemia may develop, especially with brisk diuresis, when severe cirrhosis is present, or after prolonged therapy.

Interference with adequate oral electrolyte intake will also contribute to hypokalemia. Hypokalemia may cause cardiac arrhythmia and may also sensitize or exaggerate the response of the heart to the toxic effects of digitalis (e.g., increased ventricular irritability).

Although any chloride deficit is generally mild and usually does not require specific treatment except under extraordinary circumstances (as in liver disease or renal disease), chloride replacement may be required in the treatment of metabolic alkalosis.

Dilutional hyponatremia may occur in edematous patients in hot weather; appropriate therapy is water restriction, rather than administration of salt except in rare instances when the hyponatremia is life-threatening. In actual salt depletion, appropriate replacement is the therapy of choice.

Hyperuricemia may occur or frank gout may be precipitated in certain patients receiving thiazide therapy.

In diabetic patients, dosage adjustments of insulin or oral hypoglycemic agents may be required. Hyperglycemia may occur with thiazide diuretics. Thus latent diabetes mellitus may become manifest during thiazide therapy.

The antihypertensive effects of the drug may be enhanced in the postsympathectomy patient.

If progressive renal impairment becomes evident, consider withholding or discontinuing Exforge HCT therapy or substituting other antihypertensive therapy.

Thiazides have been shown to increase the urinary excretion of magnesium; this may result in hypomagnesemia.

Thiazides may decrease urinary calcium excretion. Thiazides may cause intermittent and slight elevation of serum calcium in the absence of known disorders of calcium metabolism. Marked hypercalcemia may be evidence of hidden hyperparathyroidism. Exforge HCT should be discontinued or non-thiazide antihypertensive therapy substituted before carrying out tests for parathyroid function.

Increases in cholesterol and triglyceride levels may be associated with thiazide diuretic therapy.

5.11 Acute Myopia and Secondary Angle-Closure Glaucoma

Hydrochlorothiazide, a sulfonamide, can cause an idiosyncratic reaction, resulting in acute transient myopia and acute angle-closure glaucoma. Symptoms include acute onset of decreased visual acuity or ocular pain and typically occur within hours to weeks of drug initiation. Untreated acute angle-closure glaucoma can lead to permanent vision loss. The primary treatment is to discontinue hydrochlorothiazide as rapidly as possible. Prompt medical or surgical treatments may need to be considered if the intraocular pressure remains uncontrolled. Risk factors for developing acute angle-closure glaucoma may include a history of sulfonamide or penicillin allergy.

6 ADVERSE REACTIONS

6.1 Clinical Trials Experience

Because clinical studies are conducted under widely varying conditions, adverse reaction rates observed in the clinical studies of a drug cannot be directly compared to rates in the clinical studies of another drug and may not reflect the rates observed in clinical practice.

In the controlled trial of Exforge HCT, where only the maximum dose (10/320/25 mg) was evaluated, safety data were obtained in 582 patients with hypertension. Adverse reactions have generally been mild and transient in nature and have only infrequently required discontinuation of therapy.

The overall frequency of adverse reactions was similar between men and women, younger (<65 years) and older (>65 years) patients, and black and white patients. In the active controlled clinical trial, discontinuation because of adverse events occurred in 4.0% of patients treated with Exforge HCT 10/320/25 mg compared to 2.9% of patients treated with valsartan/HCTZ 320/25 mg, 1.6% of patients treated with amlodipine/valsartan 10/320 mg, and 3.4% of patients treated with HCTZ/amlodipine 25/10 mg. The most common reasons for discontinuation of therapy with Exforge HCT were dizziness (1.0%) and hypotension (0.7%).

The most frequent adverse events that occurred in the active controlled clinical trial in at least 2% of patients treated with Exforge HCT are presented in the table below:

Preferred Term | Aml/Val/HCTZ 10/320/25 mg N=582 n (%) | Val/HCTZ 320/25 mg N=559 n (%) | Aml/Val 10/320 mg N=566 n (%) | HCTZ/Aml 25/10 mg N=561 n (%)
Dizziness | 48 (8.2) | 40 (7.2) | 14 (2.5) | 23 (4.1)
Edema | 38 (6.5) | 8 (1.4) | 65 (11.5) | 63 (11.2)
Headache | 30 (5.2) | 31 (5.5) | 30 (5.3) | 40 (7.1)
Dyspepsia | 13 (2.2) | 5 (0.9) | 6 (1.1) | 2 (0.4)
Fatigue | 13 (2.2) | 15 (2.7) | 12 (2.1) | 8 (1.4)
Muscle spasms | 13 (2.2) | 7 (1.3) | 7 (1.2) | 5 (0.9)
Back pain | 12 (2.1) | 13 (2.3) | 5 (0.9) | 12 (2.1)
Nausea | 12 (2.1) | 7 (1.3) | 10 (1.8) | 12 (2.1)
Nasopharyngitis | 12 (2.1) | 13 (2.3) | 13 (2.3) | 12 (2.1)

Orthostatic events (orthostatic hypotension and postural dizziness) were seen in 0.5% of patients. Other adverse reactions that occurred in clinical trials with Exforge HCT (>0.2%) are listed below. It cannot be determined whether these events were causally related to Exforge HCT.

Cardiac Disorders: tachycardia

Ear and Labyrinth Disorders: vertigo, tinnitus

Eye Disorders: vision blurred

Gastrointestinal Disorders: diarrhea, abdominal pain upper, vomiting, abdominal pain, toothache, dry mouth, gastritis, hemorrhoids

General Disorders and Administration Site Conditions: asthenia, non-cardiac chest pain, chills, malaise

Infections and Infestations: upper respiratory tract infection, bronchitis, influenza, pharyngitis, tooth abscess, gastroenteritis viral, respiratory tract infection, rhinitis, urinary tract infection

Injury, Poisoning and Procedural Complications: back injury, contusion, joint sprain, procedural pain

Investigations: blood uric acid increased, blood creatine phosphokinase increased, weight decreased

Metabolism and Nutrition Disorders: hypokalaemia, diabetes mellitus, hyperlipidemia, hyponatremia

Musculoskeletal and Connective Tissue Disorders: pain in extremity, arthralgia, musculoskeletal pain, muscular weakness, musculoskeletal weakness, musculoskeletal stiffness, joint swelling, neck pain, osteoarthritis, tendonitis

Nervous System Disorders: parasthesia, somnolence, syncope, carpal tunnel syndrome, disturbance in attention, dizziness postural, dysgeusia, head discomfort, lethargy, sinus headache, tremor

Psychiatric Disorders: anxiety, depression, insomnia

Renal and Urinary Disorders: pollakiuria

Reproductive System and Breast Disorders: erectile dysfunction

Respiratory, Thoracic and Mediastinal Disorders: dyspnea, nasal congestion, cough, pharyngolaryngeal pain

Skin and Subcutaneous Tissue Disorders: pruritus, hyperhidrosis, night sweats, rash

Vascular Disorders: hypotension

Isolated cases of the following clinically notable adverse reactions were also observed in clinical trials: anorexia, constipation, dehydration, dysuria, increased appetite, viral infection.

Amlodipine

Amlodipine has been evaluated for safety in more than 11,000 patients in U.S. and foreign clinical trials. Other adverse reactions not listed above that have been reported in <1% but >0.1% of patients in controlled clinical trials or under conditions of open trials or marketing experience where a causal relationship is uncertain were:

Cardiovascular: arrhythmia (including ventricular tachycardia and atrial fibrillation), bradycardia, chest pain, peripheral ischemia, syncope, postural hypotension, vasculitis

Central and Peripheral Nervous System: neuropathy peripheral, tremor

Gastrointestinal: anorexia, dysphagia, pancreatitis, gingival hyperplasia

General: allergic reaction, hot flushes, malaise, rigors, weight gain

Musculoskeletal System: arthrosis, muscle cramps

Psychiatric: sexual dysfunction (male and female), nervousness, abnormal dreams, depersonalization

Skin and Appendages: angioedema, erythema multiforme, rash erythematous, rash maculopapular

Special Senses: abnormal vision, conjunctivitis, diplopia, eye pain, tinnitus

Urinary System: micturition frequency, micturition disorder, nocturia

Autonomic Nervous System: sweating increased

Metabolic and Nutritional: hyperglycemia, thirst

Hemopoietic: leukopenia, purpura, thrombocytopenia

Other adverse reactions reported with amlodipine at a frequency of ≤0.1% of patients include: cardiac failure, pulse irregularity, extrasystoles, skin discoloration, urticaria, skin dryness, alopecia, dermatitis, muscle weakness, twitching, ataxia, hypertonia, migraine, cold and clammy skin, apathy, agitation, amnesia, gastritis, increased appetite, loose stools, rhinitis, dysuria, polyuria, parosmia, taste perversion, abnormal visual accommodation, and xerophthalmia. Other reactions occurred sporadically and cannot be distinguished from medications or concurrent disease states such as myocardial infarction and angina.

Adverse reactions reported for amlodipine for indications other than hypertension may be found in its full prescribing information.

Valsartan

Valsartan has been evaluated for safety in more than 4,000 hypertensive patients in clinical trials. In trials in which valsartan was compared to an ACE inhibitor with or without placebo, the incidence of dry cough was significantly greater in the ACE inhibitor group (7.9%) than in the groups who received valsartan (2.6%) or placebo (1.5%). In a 129 patient trial limited to patients who had dry cough when they had previously received ACE inhibitors, the incidences of cough in patients who received valsartan, HCTZ, or lisinopril were 20%, 19%, and 69% respectively (p<0.001).

Other adverse reactions, not listed above, occurring in >0.2% of patients in controlled clinical trials with valsartan are:

Digestive: flatulence

Respiratory: sinusitis, pharyngitis

Urogenital: impotence

Adverse reactions reported for valsartan for indications other than hypertension may be found in the prescribing information for Diovan.

Hydrochlorothiazide

Other adverse reactions not listed above that have been reported with hydrochlorothiazide, without regard to causality, are listed below:

Body as a Whole: weakness

Digestive: pancreatitis, jaundice (intrahepatic cholestatic jaundice), sialadenitis, cramping, gastric irritation

Hematologic: aplastic anemia, agranulocytosis, hemolytic anemia

Hypersensitivity: photosensitivity, urticaria, necrotizing angiitis (vasculitis and cutaneous vasculitis), fever, respiratory distress including pneumonitis and pulmonary edema, anaphylactic reactions

Metabolic: glycosuria, hyperuricemia

Nervous System/Psychiatric: restlessness

Renal: renal failure, renal dysfunction, interstitial nephritis

Skin: erythema multiforme including Stevens-Johnson syndrome, exfoliative dermatitis including toxic epidermal necrolysis

Special Senses: transient blurred vision, xanthopsia.

6.2 Post-Marketing Experience

Amlodipine

With amlodipine, gynecomastia has been reported infrequently and a causal relationship is uncertain. Jaundice and hepatic enzyme elevations (mostly consistent with cholestasis or hepatitis), in some cases severe enough to require hospitalization, have been reported in association with use of amlodipine.

Valsartan

The following additional adverse reactions have been reported in post-marketing experience with valsartan or valsartan/hydrochlorothiazide:

Blood and Lymphatic: There are very rare reports of thrombocytopenia.

Hypersensitivity: There are rare reports of angioedema.

Digestive: Elevated liver enzymes and very rare reports of hepatitis

Renal: Impaired renal function

Clinical Laboratory Tests: Hyperkalemia

Dermatologic: Alopecia

Vascular: Vasculitis

Nervous System: Syncope

Rare cases of rhabdomyolysis have been reported in patients receiving angiotensin II receptor blockers. Because these reactions are reported voluntarily from a population of uncertain size, it is not always possible to reliably estimate their frequency or establish a causal relationship to drug exposure.

7 DRUG INTERACTIONS

No drug interaction studies have been conducted with Exforge HCT and other drugs, although studies have been conducted with the individual components. A pharmacokinetic drug-drug interaction study has been conducted to address the potential for pharmacokinetic interaction between the triple combination, Exforge HCT, and the corresponding three double combinations. No clinically relevant interaction was observed.

Amlodipine

In clinical trials, amlodipine has been safely administered with thiazide diuretics, beta-blockers, angiotensin-converting enzyme inhibitors, long-acting nitrates, sublingual nitroglycerin, digoxin, warfarin, non-steroidal anti-inflammatory drugs, antibiotics, and oral hypoglycemic drugs.

Cimetidine: Co-administration of amlodipine with cimetidine did not alter the pharmacokinetics of amlodipine.

Grapefruit juice: Co-administration of 240 mL of grapefruit juice with a single oral dose of amlodipine 10 mg in 20 healthy volunteers had no significant effect on the pharmacokinetics of amlodipine.

Magnesium and aluminum hydroxide (antacid): Co-administration of the magnesium and aluminum hydroxide antacid with a single dose of amlodipine had no significant effect on the pharmacokinetics of amlodipine.

Sildenafil: A single 100 mg dose of sildenafil in subjects with essential hypertension had no effect on the pharmacokinetic parameters of amlodipine. When amlodipine and sildenafil were used in combination, each agent independently exerted its own blood pressure lowering effect.

Atorvastatin: Co-administration of multiple 10 mg doses of amlodipine with 80 mg of atorvastatin resulted in no significant change in the steady state pharmacokinetic parameters of atorvastatin.

Digoxin: Co-administration of amlodipine with digoxin did not change serum digoxin levels or digoxin renal clearance in normal volunteers.

Warfarin: Co-administration of amlodipine with warfarin did not change the warfarin prothrombin response time.

Simvastatin: Co-administration of multiple doses of 10 mg of amlodipine with 80 mg simvastatin resulted in a 77% increase in exposure to simvastatin compared to simvastatin alone. Limit the dose of simvastatin in patients on amlodipine to 20 mg daily.

Valsartan

No clinically significant pharmacokinetic interactions were observed when valsartan was co-administered with amlodipine, atenolol, cimetidine, digoxin, furosemide, glyburide, hydrochlorothiazide, or indomethacin. The valsartan-atenolol combination was more antihypertensive than either component, but it did not lower the heart rate more than atenolol alone.

In vitro metabolism studies have indicated that CYP450 mediated drug interaction between valsartan and co-administered drugs are unlikely because of the low extent of metabolism [see Pharmacokinetics – Valsartan, (12.3)].

Co-administration of valsartan and warfarin did not change the pharmacokinetics of valsartan or the time-course of the anticoagulant properties of warfarin.

As with other drugs that block angiotensin II or its effects, concomitant use of potassium sparing diuretics (e.g., spironolactone, triamterene, amiloride), potassium supplements, or salt substitutes containing potassium may lead to increases in serum potassium and in heart failure patients to increases in serum creatinine.

Hydrochlorothiazide

When administered concurrently the following drugs may interact with thiazide diuretics:

Alcohol, barbiturates, or narcotics: Potentiation of orthostatic hypotension may occur.

Antidiabetic drugs (oral agents and insulin): Dosage adjustment of the antidiabetic drug may be required.

Other antihypertensive drugs: Additive effect or potentiation.

Cholestyramine and colestipol resins: Absorption of hydrochlorothiazide is impaired in the presence of anionic exchange resins. Single doses of either cholestyramine or colestipol resins bind the hydrochlorothiazide and reduce its absorption from the gastrointestinal tract by up to 85% and 43% respectively.

Corticosteroids, ACTH: Intensified electrolyte depletion, particularly hypokalemia.

Pressor amines (e.g., norepinephrine): Possible decreased response to pressor amines but not sufficient to preclude their use.

Skeletal muscle relaxants, nondepolarizing (e.g., tubocurarine): Possible increased responsiveness to the muscle relaxant.

Lithium: Should not generally be given with diuretics. Diuretic agents reduce the renal clearance of lithium and add a high risk of lithium toxicity. Refer to the package insert for lithium preparations before use of such preparations with Exforge HCT.

Non-steroidal anti-inflammatory drugs: In some patients, the administration of a non-steroidal anti-inflammatory agent can reduce the diuretic, natriuretic, and antihypertensive effects of loop, potassium-sparing and thiazide diuretics.

Carbamazepine: May lead to symptomatic hyponatremia.

7.1 Clinical Laboratory Test Findings

Clinical laboratory test findings for Exforge HCT were obtained in a controlled trial of Exforge HCT administered at the maximal dose of 10/320/25 mg compared to maximal doses of dual therapies, i.e. valsartan/HCTZ 320/25 mg, amlodipine/valsartan 10/320 mg, and HCTZ/amlodipine 25/10 mg. Findings for the components of Exforge HCT were obtained from other trials.

Creatinine: In hypertensive patients, greater than 50% increases in creatinine occurred in 2.1% of Exforge HCT patients compared to 2.4% of valsartan/HCTZ patients, 0.7% of amlodipine/valsartan patients, and 1.8% of HCTZ/amlodipine patients.

In heart failure patients, greater than 50% increases in creatinine were observed in 3.9% of valsartan-treated patients compared to 0.9% of placebo-treated patients. In post-myocardial infarction patients, doubling of serum creatinine was observed in 4.2% of valsartan-treated patients and 3.4% of captopril-treated patients.

Liver Function Tests: Occasional elevations (greater than 150%) of liver chemistries occurred in Exforge HCT-treated patients.

Blood Urea Nitrogen (BUN): In hypertensive patients, greater than 50% increases in BUN were observed in 30% of Exforge HCT-treated patients compared to 29% of valsartan/HCTZ patients, 15.8% of amlodipine/valsartan patients, and 18.5% of HCTZ/amlodipine patients. The majority of BUN values remained within normal limits.

In heart failure patients, greater than 50% increases in BUN were observed in 17% of valsartan-treated patients compared to 6% of placebo-treated patients.

Serum Electrolytes (Potassium): In hypertensive patients, greater than 20% decreases in serum potassium were observed in 6.5% of Exforge HCT-treated patients compared to 3.3% of valsartan/HCTZ patients, 0.4% of amlodipine/valsartan patients, and 19.3% of HCTZ/amlodipine patients. Greater than 20% increases in potassium were observed in 3.5% of Exforge HCT-treated patients compared to 2.4% of valsartan/HCTZ patients, 6.2% of amlodipine/valsartan patients, and 2.2% of HCTZ/amlodipine patients.

In heart failure patients, greater than 20% increases in serum potassium were observed in 10% of valsartan-treated patients compared to 5.1% of placebo-treated patients [see Warnings and Precautions, Electrolytes and Metabolic Imbalances (5.10)].

Neutropenia: Neutropenia (<1500/L) was observed in 1.9% of patients treated with valsartan and 0.8% of patients treated with placebo.

7.3 Drug/Food Interactions

The bioavailability of amlodipine, valsartan, and HCTZ were not altered when Exforge HCT was administered with food.

8 USE IN SPECIFIC POPULATIONS

8.1 Pregnancy

Pregnancy Category D

Valsartan, like other drugs that act on the renin angiotensin system, can cause fetal and neonatal morbidity and death when used during the second or third trimester of pregnancy. If Exforge HCT is used during pregnancy, or if the patient becomes pregnant while taking this drug, the patient should be apprised of the potential hazard to the fetus.

Angiotensin II receptor antagonists, like valsartan, and angiotensin converting enzyme (ACE) inhibitors exert similar effects on the renin-angiotensin system. In several dozen published cases, ACE inhibitor use during the second and third trimesters of pregnancy was associated with fetal and neonatal injury, including hypotension, neonatal skull hypoplasia, anuria, reversible or irreversible renal failure, and death. Oligohydramnios was also reported, presumably from decreased fetal renal function. In this setting, oligohydramnios was associated with fetal limb contractures, craniofacial deformation, and hypoplastic lung development. Prematurity, intrauterine growth retardation, and patent ductus arteriosus were also reported, although it is not clear whether these occurrences were due to exposure to the drug. In a retrospective study, first trimester use of ACE inhibitors, a specific class of drugs acting on the renin angiotensin system, was associated with a potential risk of birth defects.

When pregnancy occurs in a patient using Exforge HCT, the physician should discontinue Exforge HCT treatment as soon as possible. The physician should inform the patient about potential risks to the fetus based on the time of gestational exposure to Exforge HCT (first trimester only or later). If exposure occurs beyond the first trimester, an ultrasound examination should be done.

In rare cases when another antihypertensive agent can not be used to treat the pregnant patient, serial ultrasound examinations should be performed to assess the intraamniotic environment. Routine fetal testing with non-stress tests, biophysical profiles, and/or contraction stress tests may be appropriate based on gestational age and standards of care in the community. If oligohydramnios occurs in these situations, individualized decisions about continuing or discontinuing Exforge HCT treatment and about pregnancy management should be made by the patient, her physician, and experts in the management of high risk pregnancy. Patients and physicians should be aware that oligohydramnios may not appear until after the fetus has sustained irreversible injury.

Infants with histories of in utero exposure to Exforge HCT should be closely observed for hypotension, oliguria, and hyperkalemia. If oliguria occurs, these infants may require blood pressure and renal perfusion support. Exchange transfusion or dialysis may be required to reverse hypotension and/or support decreased renal function.

Healthcare professionals who prescribe drugs acting directly on the renin angiotensin system should counsel women of childbearing potential about the risks of these agents during pregnancy [see Nonclinical Toxicology (13.3)].

8.3 Nursing Mothers

It is not known whether amlodipine and valsartan are excreted in human milk, but thiazides are excreted in human milk and valsartan is excreted in rat milk. Because of the potential for adverse effects on the nursing infant, a decision should be made whether to discontinue nursing or discontinue the drug, taking into account the importance of the drug to the mother.

8.4 Pediatric Use

The safety and effectiveness of Exforge HCT in pediatric patients have not been established.

8.5 Geriatric Use

In controlled clinical trials, 82 hypertensive patients treated with Exforge HCT were ≥65 years and 13 were ≥75 years. No overall differences in the efficacy or safety of Exforge HCT were observed in this patient population, but greater sensitivity of some older individuals cannot be ruled out.

10 OVERDOSAGE

Limited data are available related to overdosage in humans. The most likely manifestations of overdosage would be hypotension and tachycardia; bradycardia could occur from parasympathetic (vagal) stimulation. If symptomatic hypotension should occur, supportive treatment should be instituted.

Amlodipine

Single oral doses of amlodipine maleate equivalent to 40 mg/kg and 100 mg/kg amlodipine in mice and rats, respectively, caused deaths. Single oral doses equivalent to 4 or more mg/kg amlodipine in dogs (11 or more times the maximum recommended human dose on a mg/m^2 basis) caused a marked peripheral vasodilation and hypotension.

Overdosage might be expected to cause excessive peripheral vasodilation with marked hypotension. In humans, experience with intentional overdosage of amlodipine is limited. Reports of intentional overdosage include a patient who ingested 250 mg and was asymptomatic and was not hospitalized; another (120 mg) who was hospitalized underwent gastric lavage and remained normotensive; the third (105 mg) was hospitalized and had hypotension (90/50 mmHg) which normalized following plasma expansion. A case of accidental drug overdose has been documented in a 19-month-old male who ingested 30 mg amlodipine (about 2 mg/kg). During the emergency room presentation, vital signs were stable with no evidence of hypotension, but a heart rate of 180 bpm. Ipecac was administered 3.5 hours after ingestion and on subsequent observation (overnight) no sequelae were noted.

If massive overdose should occur, active cardiac and respiratory monitoring should be instituted. Frequent blood pressure measurements are essential. Should hypotension occur, cardiovascular support including elevation of the extremities and the judicious administration of fluids should be initiated. If hypotension remains unresponsive to these conservative measures, administration of vasopressors (such as phenylephrine) should be considered with attention to circulating volume and urine output. Intravenous calcium gluconate may help to reverse the effects of calcium entry blockade. As amlodipine is highly protein bound, hemodialysis is not likely to be of benefit.

Valsartan

Depressed level of consciousness, circulatory collapse and shock have been reported.

Valsartan is not removed from the plasma by hemodialysis.

Valsartan was without grossly observable adverse effects at single oral doses up to 2000 mg/kg in rats and up to 1000 mg/kg in marmosets, except for the salivation and diarrhea in the rat and vomiting in the marmoset at the highest dose (60 and 31 times, respectively, the maximum recommended human dose on a mg/m^2 basis). (Calculations assume an oral dose of 320 mg/day and a 60-kg patient.)

Hydrochlorothiazide

The degree to which hydrochlorothiazide is removed by hemodialysis has not been established. The most common signs and symptoms observed in patients are those caused by electrolyte depletion (hypokalemia, hypochloremia, hyponatremia) and dehydration resulting from excessive diuresis. If digitalis has also been administered, hypokalemia may accentuate cardiac arrhythmias.

The oral LD50 of hydrochlorothiazide is greater than 10 g/kg in both mice and rats, 2000 and 4000 times, respectively, the maximum recommended human dose on a mg/m^2 basis. (Calculations assume an oral dose of 25 mg/day and a 60-kg patient.)

Valsartan and Hydrochlorothiazide

In rats and marmosets, single oral doses of valsartan up to 1524 and 762 mg/kg in combination with hydrochlorothiazide at doses up to 476 and 238 mg/kg, respectively, were very well tolerated without any treatment-related effects. These no adverse effect doses in rats and marmosets, respectively, represent 46.5 and 23 times the maximum recommended human dose (MRHD) of valsartan and 188 and 113 times the MRHD of hydrochlorothiazide on a mg/m^2 basis. (Calculations assume an oral dose of 320 mg/day valsartan in combination with 25 mg/day hydrochlorothiazide and a 60-kg patient.)

11 DESCRIPTION

Exforge HCT is a fixed combination of amlodipine, valsartan and hydrochlorothiazide.

Exforge HCT contains the besylate salt of amlodipine, a dihydropyridine calcium channel blocker (CCB). Amlodipine besylate, USP is a white to pale yellow crystalline powder, slightly soluble in water and sparingly soluble in ethanol. Amlodipine besylate’s chemical name is 3-Ethyl 5-methyl (±)-2-[(2-aminoethoxy)methyl]-4-(o-chlorophenyl)-1,4-dihydro-6-methyl-3,5-pyridinedicarboxylate, monobenzenesulfonate ; its structural formula is

Its empirical formula is C20H25ClN2O5•C6H6O3S and its molecular weight is 567.1.

Valsartan, USP is a nonpeptide, orally active, and specific angiotensin II antagonist acting on the AT1 receptor subtype. Valsartan is a white to practically white fine powder, soluble in ethanol and methanol and slightly soluble in water. Valsartan’s chemical name is N-(1-oxopentyl)-N-[[2′-(1H-tetrazol-5-yl) [1,1′-biphenyl]-4-yl]methyl]-L-valine; its structural formula is

Its empirical formula is C24H29N5O3 and its molecular weight is 435.5.

Hydrochlorothiazide, USP is a white, or practically white, practically odorless, crystalline powder. It is slightly soluble in water; freely soluble in sodium hydroxide solution, in n-butylamine, and in dimethylformamide; sparingly soluble in methanol; and insoluble in ether, in chloroform, and in dilute mineral acids. Hydrochlorothiazide is chemically described as 6-chloro-3,4-dihydro-2H-1,2,4-benzothiadiazine-7- sulfonamide 1,1-dioxide.

Hydrochlorothiazide is a thiazide diuretic. Its empirical formula is C7H8ClN3O4S2, its molecular weight is 297.73, and its structural formula is

Exforge HCT film-coated tablets are formulated in five strengths for oral administration with a combination of amlodipine besylate, valsartan and hydrochlorothiazide, providing for the following available combinations: 5/160/12.5 mg, 10/160/12.5 mg, 5/160/25 mg, 10/160/25 mg and 10/320/25 mg amlodipine besylate/valsartan/hydrochlorothiazide. The inactive ingredients for all strengths of the tablets include microcrystalline cellulose; crospovidone; colloidal anhydrous silica; magnesium stearate; hypromellose, macrogol 4000 and talc. Additionally, the 5/160/12.5 mg strength contains titanium dioxide; the 10/160/12.5 mg strength contains titanium dioxide and yellow and red iron oxides; the 5/160/25 mg strength contains titanium dioxide and yellow iron oxide and the 10/160/25 mg and 10/320/25 mg strengths both contain yellow iron oxide.

12 CLINICAL PHARMACOLOGY

12.1 Mechanism of Action

The active ingredients of Exforge HCT target three separate mechanisms involved in blood pressure regulation. Specifically, amlodipine blocks the contractile effects of calcium on cardiac and vascular smooth muscle cells; valsartan blocks the vasoconstriction and sodium retaining effects of angiotensin II on cardiac, vascular smooth muscle, adrenal and renal cells; and hydrochlorothiazide directly promotes the excretion of sodium and chloride in the kidney leading to reductions in intravascular volume. A more detailed description of the mechanism of action of each individual component follows.

Amlodipine

Amlodipine is a dihydropyridine calcium channel blocker that inhibits the transmembrane influx of calcium ions into vascular smooth muscle and cardiac muscle. Experimental data suggest that amlodipine binds to both dihydropyridine and nondihydropyridine binding sites. The contractile processes of cardiac muscle and vascular smooth muscle are dependent upon the movement of extracellular calcium ions into these cells through specific ion channels. Amlodipine inhibits calcium ion influx across cell membranes selectively, with a greater effect on vascular smooth muscle cells than on cardiac muscle cells. Negative inotropic effects can be detected in vitro but such effects have not been seen in intact animals at therapeutic doses. Serum calcium concentration is not affected by amlodipine. Within the physiologic pH range, amlodipine is an ionized compound (pKa=8.6), and its kinetic interaction with the calcium channel receptor is characterized by a gradual rate of association and dissociation with the receptor binding site, resulting in a gradual onset of effect.

Amlodipine is a peripheral arterial vasodilator that acts directly on vascular smooth muscle to cause a reduction in peripheral vascular resistance and reduction in blood pressure.

Valsartan

Angiotensin II is formed from angiotensin I in a reaction catalyzed by angiotensin-converting enzyme (ACE, kininase II). Angiotensin II is the principal pressor agent of the renin-angiotensin system, with effects that include vasoconstriction, stimulation of synthesis and release of aldosterone, cardiac stimulation, and renal reabsorption of sodium. Valsartan blocks the vasoconstrictor and aldosterone-secreting effects of angiotensin II by selectively blocking the binding of angiotensin II to the AT1 receptor in many tissues, such as vascular smooth muscle and the adrenal gland. Its action is therefore independent of the pathways for angiotensin II synthesis.

There is also an AT2 receptor found in many tissues, but AT2 is not known to be associated with cardiovascular homeostasis. Valsartan has much greater affinity (about 20,000-fold) for the AT1 receptor than for the AT2 receptor. The increased plasma levels of angiotensin following AT1 receptor blockade with valsartan may stimulate the unblocked AT2 receptor. The primary metabolite of valsartan is essentially inactive with an affinity for the AT1 receptor about one-200th that of valsartan itself.

Blockade of the renin-angiotensin system with ACE inhibitors, which inhibit the biosynthesis of angiotensin II from angiotensin I, is widely used in the treatment of hypertension. ACE inhibitors also inhibit the degradation of bradykinin, a reaction also catalyzed by ACE. Because valsartan does not inhibit ACE (kininase II), it does not affect the response to bradykinin. Whether this difference has clinical relevance is not yet known. Valsartan does not bind to or block other hormone receptors or ion channels known to be important in cardiovascular regulation.

Blockade of the angiotensin II receptor inhibits the negative regulatory feedback of angiotensin II on renin secretion, but the resulting increased plasma renin activity and angiotensin II circulating levels do not overcome the effect of valsartan on blood pressure.

Hydrochlorothiazide

Hydrochlorothiazide is a thiazide diuretic. Thiazides affect the renal tubular mechanisms of electrolyte reabsorption, directly increasing excretion of sodium and chloride in approximately equivalent amounts. Indirectly, the diuretic action of hydrochlorothiazide reduces plasma volume, with consequent increases in plasma renin activity, increases in aldosterone secretion, increases in urinary potassium loss, and decreases in serum potassium. The renin-aldosterone link is mediated by angiotensin II, so coadministration of an angiotensin II receptor antagonist tends to reverse the potassium loss associated with these diuretics.

The mechanism of the antihypertensive effect of thiazides is unknown.

12.2 Pharmacodynamics

Exforge HCT has been shown to be effective in lowering blood pressure. The three components of Exforge HCT (amlodipine, valsartan, hydrochlorothiazide) lower the blood pressure through complementary mechanisms, each working at a separate site and blocking different effector pathways. The pharmacodynamics of each individual component is described below.

Exforge HCT has not been studied in indications other than hypertension.

Amlodipine

Following administration of therapeutic doses to patients with hypertension, amlodipine produces vasodilation resulting in a reduction of supine and standing blood pressures. These decreases in blood pressure are not accompanied by a significant change in heart rate or plasma catecholamine levels with chronic dosing. Although the acute intravenous administration of amlodipine decreases arterial blood pressure and increases heart rate in hemodynamic studies of patients with chronic stable angina, chronic oral administration of amlodipine in clinical trials did not lead to clinically significant changes in heart rate or blood pressures in normotensive patients with angina.

With chronic once daily administration, antihypertensive effectiveness is maintained for at least 24 hours. Plasma concentrations correlate with effect in both young and elderly patients. The magnitude of reduction in blood pressure with amlodipine is also correlated with the height of pretreatment elevation; thus, individuals with moderate hypertension (diastolic pressure 105-114 mmHg) had about a 50% greater response than patients with mild hypertension (diastolic pressure 90-104 mmHg). Normotensive subjects experienced no clinically significant change in blood pressure (+1/-2 mmHg).

In hypertensive patients with normal renal function, therapeutic doses of amlodipine resulted in a decrease in renal vascular resistance and an increase in glomerular filtration rate and effective renal plasma flow without change in filtration fraction or proteinuria.

As with other calcium channel blockers, hemodynamic measurements of cardiac function at rest and during exercise (or pacing) in patients with normal ventricular function treated with amlodipine have generally demonstrated a small increase in cardiac index without significant influence on dP/dt or on left ventricular end diastolic pressure or volume. In hemodynamic studies, amlodipine has not been associated with a negative inotropic effect when administered in the therapeutic dose range to intact animals and man, even when co-administered with beta-blockers to man. Similar findings, however, have been observed in normals or well-compensated patients with heart failure with agents possessing significant negative inotropic effects.

Amlodipine does not change sinoatrial nodal function or atrioventricular conduction in intact animals or man. In patients with chronic stable angina, intravenous administration of 10 mg did not significantly alter A-H and H-V conduction and sinus node recovery time after pacing. Similar results were obtained in patients receiving amlodipine and concomitant beta-blockers. In clinical studies in which amlodipine was administered in combination with beta-blockers to patients with either hypertension or angina, no adverse effects of electrocardiographic parameters were observed. In clinical trials with angina patients alone, amlodipine therapy did not alter electrocardiographic intervals or produce higher degrees of AV blocks.

Amlodipine has indications other than hypertension which are described in its full prescribing information.

Valsartan

Valsartan inhibits the pressor effect of angiotensin II infusions. An oral dose of 80 mg inhibits the pressor effect by about 80% at peak with approximately 30% inhibition persisting for 24 hours. No information on the effect of larger doses is available.

Removal of the negative feedback of angiotensin II causes a 2- to 3-fold rise in plasma renin and consequent rise in angiotensin II plasma concentration in hypertensive patients. Minimal decreases in plasma aldosterone were observed after administration of valsartan; very little effect on serum potassium was observed.

In multiple dose studies in hypertensive patients with stable renal insufficiency and patients with renovascular hypertension, valsartan had no clinically significant effects on glomerular filtration rate, filtration fraction, creatinine clearance, or renal plasma flow.

Administration of valsartan to patients with essential hypertension results in a significant reduction of sitting, supine, and standing systolic blood pressure, usually with little or no orthostatic change.

Valsartan has indications other than hypertension which are described in its full prescribing information.

Hydrochlorothiazide

After oral administration of hydrochlorothiazide, diuresis begins within 2 hours, peaks in about 4 hours and lasts about 6 to 12 hours.

12.3 Pharmacokinetics

Exforge HCT

Following oral administration of Exforge HCT in normal healthy adults, peak plasma concentrations of amlodipine, valsartan and HCTZ are reached in about 6 hours, 3 hours, and 2 hours, respectively. The rate and extent of absorption of amlodipine, valsartan and HCTZ from Exforge HCT are the same as when administered as individual dosage forms.

Amlodipine

Peak plasma concentrations of amlodipine are reached 6-12 hours after administration of amlodipine alone. Absolute bioavailability has been estimated to be between 64% and 90%. The apparent volume of distribution of amlodipine is 21 L/kg. Approximately 93% of circulating amlodipine is bound to plasma proteins in hypertensive patients.

Amlodipine is extensively (about 90%) converted to inactive metabolites via hepatic metabolism with 10% of the parent compound and 60% of the metabolites excreted in the urine.

Elimination of amlodipine from the plasma is biphasic with a terminal elimination half-life of about 30-50 hours. Steady state plasma levels of amlodipine are reached after 7 to 8 days of consecutive daily dosing.

Valsartan

Following oral administration of valsartan alone peak plasma concentrations of valsartan are reached in 2 to 4 hours. Absolute bioavailability is about 25% (range 10%-35%).

The steady state volume of distribution of valsartan after intravenous administration is 17 L indicating that valsartan does not distribute into tissues extensively. Valsartan is highly bound to serum proteins (95%), mainly serum albumin.

Valsartan shows bi-exponential decay kinetics following intravenous administration with an average elimination half-life of about 6 hours. The recovery is mainly as unchanged drug, with only about 20% of dose recovered as metabolites. The primary metabolite, accounting for about 9% of dose, is valeryl 4-hydroxy valsartan. In vitro metabolism studies involving recombinant CYP450 enzymes indicated that the CYP2C9 isoenzyme is responsible for the formation of valeryl-4-hydroxy valsartan. Valsartan does not inhibit CYP450 isozymes at clinically relevant concentrations. CYP450 mediated drug interaction between valsartan and co-administered drugs are unlikely because of the low extent of metabolism.

Valsartan, when administered as an oral solution, is primarily recovered in feces (about 83% of dose) and urine (about 13% of dose). Following intravenous administration, plasma clearance of valsartan is about 2 L/h and its renal clearance is 0.62 L/h (about 30% of total clearance).

Hydrochlorothiazide

Hydrochlorothiazide is not metabolized but is eliminated rapidly by the kidney. At least 61% of the oral dose is eliminated as unchanged drug within 24 hours. The elimination half-life is between 5.8 and 18.9 hours. Hydrochlorothiazide crosses the placental but not the blood-brain barrier and is excreted in breast milk.

Geriatric

Studies with amlodipine: Elderly patients have decreased clearance of amlodipine with a resulting increase in AUC of approximately 40%-60%; therefore a lower initial dose of amlodipine may be required.

Studies with valsartan: Exposure (measured by AUC) to valsartan is higher by 70% and the half-life is longer by 35% in the elderly than in the young. No dosage adjustment is necessary.

Gender

Studies with valsartan: Pharmacokinetics of valsartan does not differ significantly between males and females.

Renal Insufficiency

Studies with amlodipine: The pharmacokinetics of amlodipine is not significantly influenced by renal impairment. Patients with renal failure may therefore receive the usual initial dose.

Studies with valsartan: There is no apparent correlation between renal function (measured by creatinine clearance) and exposure (measured by AUC) to valsartan in patients with different degrees of renal impairment. Consequently, dose adjustment is not required in patients with mild-to-moderate renal dysfunction. No studies have been performed in patients with severe impairment of renal function (creatinine clearance <10 mL/min). Valsartan is not removed from the plasma by hemodialysis. In the case of severe renal disease, exercise care with dosing of valsartan.

Studies with hydrochlorothiazide: The half-life of hydrochlorothiazide elimination was lengthened to 21 hours in a study of patients with impaired renal function (mean creatinine clearance of 19 mL/min).

Hepatic Insufficiency

Studies with amlodipine: Patients with hepatic insufficiency have decreased clearance of amlodipine with resulting increase in AUC of approximately 40%-60%; therefore, a lower initial dose of amlodipine may be required.

Studies with valsartan: On average, patients with mild-to-moderate chronic liver disease have twice the exposure (measured by AUC values) to valsartan of healthy volunteers (matched by age, sex and weight). In general, no dosage adjustment is needed in patients with mild-to-moderate liver disease. Care should be exercised in patients with liver disease.

13 NONCLINICAL TOXICOLOGY

13.1 Carcinogenesis, Mutagenesis, Impairment of Fertility

Studies with amlodipine/valsartan/hydrochlorothiazide: No carcinogenicity, mutagenicity or fertility studies have been conducted with this combination. However, these studies have been conducted for amlodipine, valsartan and hydrochlorothiazide alone. Based on the preclinical safety and human pharmacokinetic studies, there is no indication of any toxicologically significant adverse interaction between these components.

Studies with amlodipine: Rats and mice treated with amlodipine maleate in the diet for up to two years, at concentrations calculated to provide daily dosage levels of 0.5, 1.25, and 2.5 mg amlodipine/kg/day, showed no evidence of a carcinogenic effect of the drug. For the mouse, the highest dose was, on mg/m^2 basis, similar to the maximum recommended human dose [MRHD] of 10 mg amlodipine/day. For the rat, the highest dose was, on a mg/m^2 basis, about two and a half times the MRHD. (Calculations based on a 60 kg patient.)

Mutagenicity studies conducted with amlodipine maleate revealed no drug-related effects at either the gene or chromosome level.

There was no effect on the fertility of rats treated orally with amlodipine maleate (males for 64 days and females for 14 days prior to mating) at doses of up to 10 mg amlodipine/kg/day (about 10 times the MRHD of 10 mg/day on a mg/m^2 basis).

Studies with valsartan: There was no evidence of carcinogenicity when valsartan was administered in the diet to mice and rats for up to 2 years at concentrations calculated to provide doses of up to 160 and 200 mg/kg/day, respectively. These doses in mice and rats are about 2.4 and 6 times, respectively, the MRHD of 320 mg/day on a mg/m^2 basis. (Calculations based on a 60 kg patient.)

Mutagenicity assays did not reveal any valsartan-related effects at either the gene or chromosome level. These assays included bacterial mutagenicity tests with Salmonella and E. coli, a gene mutation test with Chinese hamster V79 cells, a cytogenetic test with Chinese hamster ovary cells, and a rat micronucleus test.

Valsartan had no adverse effects on the reproductive performance of male or female rats at oral doses of up to 200 mg/kg/day. This dose is about 6 times the maximum recommended human dose on a mg/m^2 basis.

Studies with hydrochlorothiazide: Two-year feeding studies in mice and rats conducted under the auspices of the National Toxicology Program (NTP) uncovered no evidence of a carcinogenic potential of hydrochlorothiazide in female mice (at doses of up to approximately 600 mg/kg/day) or in male and female rats (at doses of up to approximately 100 mg/kg/day). The NTP, however, found equivocal evidence for hepatocarcinogenicity in male mice.

Hydrochlorothiazide was not genotoxic in vitro in the Ames mutagenicity assay of Salmonella Typhimurium strains TA 98, TA 100, TA 1535, TA 1537, and TA 1538 and in the Chinese Hamster Ovary (CHO) test for chromosomal aberrations, or in vivo in assays using mouse germinal cell chromosomes, Chinese hamster bone marrow chromosomes, and the Drosophila sex-linked recessive lethal trait gene. Positive test results were obtained in the in vitro CHO Sister Chromatid Exchange (clastogenicity) and Mouse Lymphoma Cell (mutagenicity) assays and in the Aspergillus Nidulans non-disjunction assay.

Hydrochlorothiazide had no adverse effects on the fertility of mice and rats of either sex in studies wherein these species were exposed via diet at doses of up to 100 and 4 mg/kg, respectively, prior to mating and throughout gestation. These doses of hydrochlorothiazide in mice and rats are 19 and 1.5 times, respectively, the maximum recommended human dose on a mg/m^2 basis. (Calculations assume an oral dose of 25 mg/day and a 60-kg patient.)

13.3 Developmental Toxicity

Studies with amlodipine: No evidence of teratogenicity or other embryo/fetal toxicity was found when pregnant rats and rabbits were treated orally with amlodipine maleate at doses of up to 10 mg amlodipine/kg/day (respectively, about 10 and 20 times the maximum recommended human dose [MRHD] of 10 mg amlodipine on a mg/m^2 basis) during their respective periods of major organogenesis. (Calculations based on a patient weight of 60 kg.) However, litter size was significantly decreased (by about 50%) and the number of intrauterine deaths was significantly increased (about 5-fold) for rats receiving amlodipine maleate at a dose equivalent to 10 mg amlodipine/kg/day for 14 days before mating and throughout mating and gestation. Amlodipine maleate has been shown to prolong both the gestation period and the duration of labor in rats at this dose. There are no adequate and well controlled studies in pregnant women.

Studies with valsartan: No teratogenic effects were observed when valsartan was administered to pregnant mice and rats at oral doses of up to 600 mg/kg/day and to pregnant rabbits at oral doses of up to 10 mg/kg/day. However, significant decreases in fetal weight, pup birth weight, pup survival rate, and slight delays in developmental milestones were observed in studies in which parental rats were treated with valsartan at oral, maternally toxic (reduction in body weight gain and food consumption) doses of 600 mg/kg/day during organogenesis or late gestation and lactation. In rabbits, fetotoxicity (i.e., resorptions, litter loss, abortions, and low body weight) associated with maternal toxicity (mortality) was observed at doses of 5 and 10 mg/kg/day. The no observed adverse effect doses of 600, 200 and 2 mg/kg/day in mice, rats and rabbits, respectively, are about 9, 6 and 0.1 times the MRHD of 320 mg/day on a mg/m^2 basis. (Calculations based on a patient weight of 60 kg.)

Studies with hydrochlorothiazide: Under the auspices of the National Toxicology Program, pregnant mice and rats that received hydrochlorothiazide via gavage at doses up to 3000 and 1000 mg/kg/day, respectively, on gestation days 6 through 15 showed no evidence of teratogenicity. These doses of hydrochlorothiazide in mice and rats are 608 and 405 times, respectively, the maximum recommended human dose on a mg/m^2 basis. (Calculations assume an oral dose of 25 mg/day and a 60-kg patient.)

Studies with amlodipine and valsartan: In the oral embryo-fetal development study in rats using amlodipine besylate plus valsartan at doses equivalent to 5 mg/kg/day amlodipine plus 80 mg/kg/day valsartan, 10 mg/kg/day amlodipine plus 160 mg/kg/day valsartan, and 20 mg/kg/day amlodipine plus 320 mg/kg/day valsartan, treatment-related maternal and fetal effects (developmental delays and alterations noted in the presence of significant maternal toxicity) were noted with the high dose combination. The no-observed-adverse-effect level (NOAEL) for embryo- fetal effects was 10 mg/kg/day amlodipine plus 160 mg/kg/day valsartan. On a systemic exposure [AUC(0-∞)] basis, these doses are, respectively, 4.3 and 2.7 times the systemic exposure [AUC(0-∞)] in humans receiving the MRHD (10/320 mg/60 kg).

Studies with valsartan and hydrochlorothiazide: There was no evidence of teratogenicity in mice, rats, or rabbits treated orally with valsartan at doses up to 600, 100 and 10 mg/kg/day, respectively, in combination with hydrochlorothiazide at doses up to 188, 31 and 3 mg/kg/day. These non-teratogenic doses in mice, rats and rabbits are, respectively, 9, 3.5 and 0.5 times the maximum recommended human dose (MRHD) of valsartan and 38, 13 and 2 times the MRHD of hydrochlorothiazide on a mg/m^2 basis. (Calculations assume an oral dose of 320 mg/day valsartan in combination with 25 mg/day hydrochlorothiazide in a 60-kg patient.)

Fetotoxicity was observed in association with maternal toxicity in rats at valsartan/hydrochlorothiazide doses ≥200/63 mg/kg/day and in rabbits at valsartan/hydrochlorothiazide doses of 10/3 mg/kg/day. Evidence of fetotoxicity in rats consisted of decreased fetal weight and fetal variations of sternebrae, vertebrae, ribs and/or renal papillae. Evidence of fetotoxicity in rabbits included increased numbers of late resorptions with resultant increases in total resorptions, postimplantation losses and decreased number of live fetuses. The no observed adverse effect doses of the valsartan/hydrochlorothiazide combination in mice, rats and rabbits were 600/188, 100/31 and 3/1 mg/kg/day, respectively. These doses in mice, rats and rabbits are, respectively, 9, 3 and 0.18 times the MRHD of valsartan and 38, 13 and 0.5 times the MRHD of hydrochlorothiazide on a mg/m^2 basis. (Calculations assume an oral dose of 320 mg/day valsartan in combination with 25 mg/day hydrochlorothiazide in a 60-kg patient.)

14 CLINICAL STUDIES

Exforge HCT was studied in a double-blind, active controlled study in hypertensive patients. A total of 2,271 patients with moderate to severe hypertension (mean baseline systolic/diastolic blood pressure was 170/107 mmHg) received treatments of amlodipine/valsartan/HCTZ 10/320/25 mg, valsartan/HCTZ 320/25 mg, amlodipine/valsartan 10/320 mg, or HCTZ/amlodipine 25/10 mg. At study initiation patients assigned to the two-component arms received lower doses of their treatment combination while patients assigned to the Exforge HCT arm received 160/12.5 mg valsartan/hydrochlorothiazide. After one week, Exforge HCT patients were titrated to 5/160/12.5 mg amlodipine/valsartan/hydrochlorothiazide, while all other patients continued receiving their initial doses. After two weeks, all patients were titrated to their full treatment dose. A total of 55% of patients were male, 14% were 65 years or older, 72% were Caucasian, and 17% were Black.

At week 8, the triple combination therapy produced greater reductions in blood pressure than each of the three dual combination treatments (p<0.0001 for both diastolic and systolic blood pressures reductions). The reductions in systolic/diastolic blood pressure with Exforge HCT were 7.6/5.0 mmHg greater than with valsartan/HCTZ, 6.2/3.3 mmHg greater than with amlodipine/valsartan, and 8.2/5.3 mmHg greater than with amlodipine/HCTZ (see Figure 1). The full blood pressure lowering effect was achieved 2 weeks after being on the maximal dose of Exforge HCT (see Figure 2 and Figure 3). As the pivotal study was an active controlled trial, the treatment effects shown in Figure 1, 2, and 3 include a placebo effect of unknown size.

Figure 1: Reduction in Mean Blood Pressure at Endpoint
Figure 2: Mean Sitting Diastolic Blood Pressure by Treatment and Week
Figure 3: Mean Sitting Systolic Blood Pressure by Treatment and Week

A subgroup of 283 patients was studied with ambulatory blood pressure monitoring. The blood pressure lowering effect in the triple therapy group was maintained throughout the 24-hour period (see Figure 4 and Figure 5).

Figure 4: Mean Ambulatory Diastolic Blood Pressure at Endpoint by Treatment and Hour
Figure 5: Mean Ambulatory Systolic Blood Pressure at Endpoint by Treatment and Hour

16 HOW SUPPLIED/STORAGE AND HANDLING

Exforge HCT (amlodipine, valsartan, hydrochlorothiazide) is available as film-coated tablets containing amlodipine besylate equivalent to 10 mg of amlodipine free-base with valsartan 320 mg and hydrochlorothiazide 25 mg, providing for the following available combination: 10/320/25 mg.

10 mg amlodipine /320 mg valsartan /25 mg hydrochlorothiazide Tablets – Brown-yellow, non-scored, film-coated tablet, ovaloid, biconvex with beveled edge with debossing “NVR” on one side and “VFL” on the other side.

Bottles of 30 | NDC 54868-6123-0

Store at 25°C (77°F); excursions permitted to 15-30°C (59-86°F), [see USP controlled room temperature.]

Protect from moisture.

Dispense in tight container (USP).

17 PATIENT COUNSELING INFORMATION

Pregnancy: Female patients of childbearing age should be told that use of drugs like Exforge HCT that act on the renin-angiotensin system during pregnancy can cause serious problems in the fetus and infant including: low blood pressure, poor development of skull bones, kidney failure and death. Discuss other treatment options with female patients planning to become pregnant. Women using Exforge HCT who become pregnant should notify their physician as soon as possible.

Symptomatic Hypotension: A patient receiving Exforge HCT should be cautioned that lightheadedness can occur, especially during the first days of therapy, and that it should be reported to the prescribing physician. The patients should be told that if syncope occurs, Exforge HCT should be discontinued until the physician has been consulted.

All patients should be cautioned that inadequate fluid intake, excessive perspiration, diarrhea, or vomiting can lead to an excessive fall in blood pressure, with the same consequences of lightheadedness and possible syncope.

Potassium Supplements: A patient receiving Exforge HCT should be told not to use potassium supplements or salt substitutes containing potassium without consulting the prescribing physician.

Information for Patients

Patient Information

Exforge HCT (X-phorj HCT)
(amlodipine and valsartan and hydrochlorothiazide) Tablets

Read the Patient Information that comes with EXFORGE HCT before you start taking it and each time you get a refill. There may be new information. This leaflet does not take the place of talking with your doctor about your medical condition or treatment.

What is the most important information I should know about EXFORGE HCT?

If you become pregnant while taking EXFORGE HCT, stop taking EXFORGE HCT and call your doctor right away. EXFORGE HCT can harm an unborn baby causing injury or death. Talk to your doctor about other treatment options to lower your blood pressure before taking EXFORGE HCT if you plan to become pregnant.

What is EXFORGE HCT?

EXFORGE HCT contains three prescription medicines:

1. amlodipine, a calcium channel blocker
2. valsartan, an angiotensin receptor blocker, and
3. hydrochlorothiazide, a diuretic (water pill)

EXFORGE HCT may be used to lower blood pressure in adults when two medicines to lower your high blood pressure are not enough.

EXFORGE HCT has not been studied in children under 18 years of age.

Who should not take EXFORGE HCT?

Do not take EXFORGE HCT if you have low or no urine output (anuria).

What should I tell my doctor before taking EXFORGE HCT?

Tell your doctor about all of your medical conditions, including if you:

- are pregnant or plan to become pregnant. See “What is the most important information I should know about EXFORGE HCT?”
- are breast-feeding or plan to breast-feed. EXFORGE HCT may pass into your milk. Do not breast-feed while you are taking EXFORGE HCT.
- are allergic to any of the ingredients in EXFORGE HCT. See the end of this leaflet for a list of the ingredients in EXFORGE HCT.
- have heart problems
- have liver problems
- have kidney problems
- are vomiting or having a lot of diarrhea
- have or had gallstones
- have Lupus

Tell your doctor about all the medicines you take, including prescription and nonprescription medicines, vitamins, and herbal supplements. Some of your other medicines and EXFORGE HCT could affect each other, causing serious side effects.

Especially tell your doctor if you take:

- other medicines for high blood pressure or a heart problem
- water pills (“diuretics”)
- potassium supplements or using a salt substitute containing potassium
- diabetes medicine including insulin
- narcotic pain medicines
- sleeping pills and anti-seizure medicines called barbiturates
- lithium, a medicine used to treat some types of depression
- aspirin or other medicines called non-steriodal anti-inflammatory drugs (NSAIDs)
- steroids
- cholesterol lowering medicine
- alcohol

Know the medicines you take. Keep a list of your medicines and show it to your doctor or pharmacist when you get a new medicine.

How should I take EXFORGE HCT?

- Take EXFORGE HCT exactly as your doctor tells you.
- Take EXFORGE HCT one time each day.
- EXFORGE HCT can be taken with or without food.
- If you miss a dose, take it as soon as you remember. If it is close to your next dose, do not take the missed dose. Just take the next dose at the regular time.
- If you take too much EXFORGE HCT, call your doctor or Poison Control Center, or go to the emergency room.
- Tell all your doctors and dentist you are taking EXFORGE HCT. This is especially important if you:
  - are going to have surgery
  - go for kidney dialysis

What are the possible side effects of EXFORGE HCT?

EXFORGE HCT may cause serious side effects including:

- harm to an unborn baby causing injury or death. See “What is the most important information I should know about EXFORGE HCT?”
- low blood pressure (hypotension). Low blood pressure is most likely to happen if you:
  - take water pills
  - are on a low salt diet
  - have heart problems
  - get dialysis treatments
  - get sick with vomiting or diarrhea
  - drink alcohol.

Lie down if you feel faint or dizzy. If you faint (lose consciousness), stop taking EXFORGE HCT. Call your doctor right away.

- Get emergency help if you get worse chest pain or chest pain that does not go away.
- kidney problems. Kidney problems may become worse in people that already have kidney disease. Some people will have changes in blood tests for kidney function and may need a lower dose of EXFORGE HCT. Call your doctor if you have swelling in your feet, ankles, or hands, or unexplained weight gain. If you have heart failure, your doctor should check your kidney function before prescribing EXFORGE HCT.
- laboratory blood test changes in people with congestive heart failure. Some people with congestive heart failure who take valsartan, one of the medicines in EXFORGE HCT, have changes in blood tests including increased potassium and decreased kidney function.
- allergic reactions
- skin rash. Call your doctor right away if you get an unusual skin rash.
- eye problems. One of the medicines in EXFORGE HCT can cause eye problems that may lead to vision loss. Symptoms of eye problems can happen within hours to weeks of starting EXFORGE HCT. Tell your doctor right away if you have:
  - decrease in vision
  - eye pain

The most common side effects of EXFORGE HCT include:

- dizziness
- swelling (edema) of the hands, ankles, or feet
- headache
- indigestion
- tiredness
- muscle spasms
- back pain
- nausea.

Tell your doctor if you have any side effect that bothers you or that does not go away.

These are not all the possible side effects of EXFORGE HCT. For more information, ask your doctor or pharmacist.

Call your doctor for medical advice about side effects. You may report side effects to FDA at 1-800-FDA-1088.

How should I store EXFORGE HCT?

- Store EXFORGE HCT at room temperature between 59°F to 86°F (15°C to 30°C).
- Keep EXFORGE HCT dry (protect it from moisture).

Keep EXFORGE HCT and all medicines out of the reach of children.

General Information about EXFORGE HCT

Medicines are sometimes prescribed for conditions that are not mentioned in the patient information leaflet. Do not use EXFORGE HCT for a condition for which it was not prescribed. Do not give EXFORGE HCT to other people, even if they have the same symptoms that you have. It may harm them.

This patient information leaflet summarizes the most important information about EXFORGE HCT. If you would like more information about EXFORGE HCT, talk with your doctor. You can ask your doctor or pharmacist for information about EXFORGE HCT that is written for health professionals. For more information go to www.EXFORGE.com or call 1-888-839-3674.

What are the ingredients in EXFORGE HCT?

Active ingredients: amlodipine besylate, valsartan and hydrochlorothiazide

The inactive ingredients of all strengths of the tablets are crospovidone, magnesium stearate, microcrystalline cellulose, and colloidal anhydrous silica. The film coating contains hypromellose, talc, macrogol 4000 and may contain titanium dioxide or yellow and red iron oxides.

What is high blood pressure (hypertension)?

Blood pressure is the force of blood in your blood vessels when your heart beats and when your heart rests. You have high blood pressure when the force is too much. EXFORGE HCT can help your blood vessels relax so your blood pressure is lower. Drugs that lower blood pressure lower your chance of having a stroke or heart attack.

High blood pressure makes the heart work harder to pump blood throughout the body and causes damage to blood vessels. If high blood pressure is not treated, it can lead to stroke, heart attack, heart failure, kidney failure and vision problems.

Distributed by:

Novartis Pharmaceuticals Corporation

East Hanover, New Jersey 07936

© Novartis

T2011-134/T2011-97

October 2011/February 2011

Additional barcode label applied by:
Physicians Total Care, Inc.
Tulsa, Oklahoma 74146

PACKAGE LABEL

PRINCIPAL DISPLAY PANEL

Package Label – 10 mg / 320 mg / 25 mg

Rx Only

Exforge HCT®

(amlodipine, valsartan, hydrochlorothiazide)

10 mg* / 320 mg / 25 mg

*each tablet contains 13.9 mg of amlodipine besylate

30 Tablets